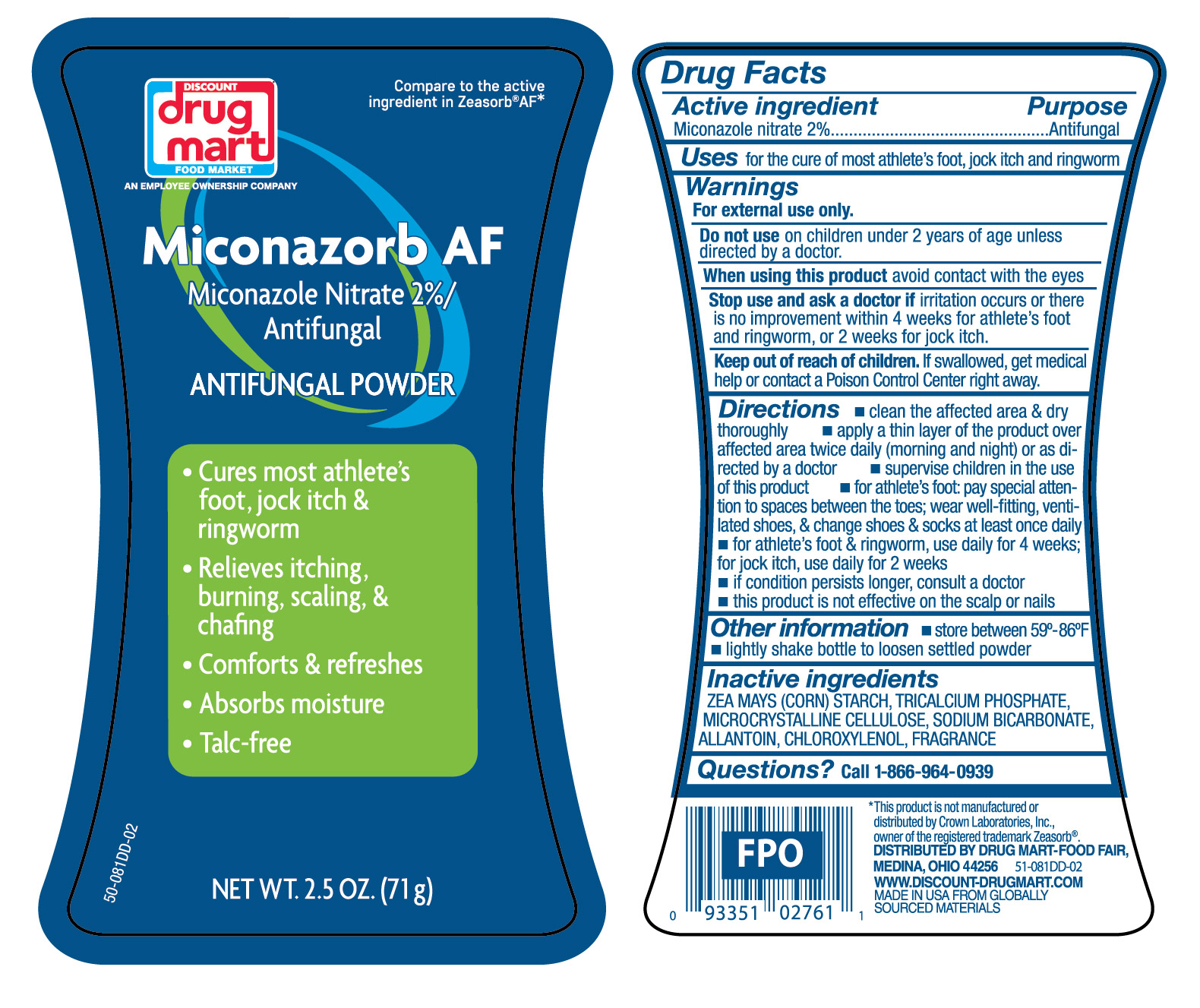 DRUG LABEL: Miconazole Nitrate
NDC: 53943-976 | Form: POWDER
Manufacturer: Discount Drug Mart, Inc
Category: otc | Type: HUMAN OTC DRUG LABEL
Date: 20251029

ACTIVE INGREDIENTS: MICONAZOLE NITRATE 20 mg/1 g
INACTIVE INGREDIENTS: CHLOROXYLENOL; SODIUM BICARBONATE; MICROCRYSTALLINE CELLULOSE; TRICALCIUM PHOSPHATE; ZEA MAYS (CORN) STARCH; ALLANTOIN

Discount Drug Mart Miconazorb Antifungal Powder Talc-Free

Active ingredient

Miconazole nitrate 2%

Purpose

Antifungal

Uses

for the cure of most athlete's foot, jock itch and ringworm

Warnings

For external use only.

Do not use

on children 2 years of age unless directed by a doctor.

When using this product

avoid contact with the eyes

Stop and ask a doctor if

irritation occurs or there is no improvement within 4 weeks for athlete's foot and ringworm, or 2 weeks for jock itch.

Keep out of reach of children.

If swallowed, get medical help or contact a Poison Control Center right away.

Directions

- clean the affected area & dry thoroughly
- apply a thin layer of the product over affected area twice daily (morning and night) or as directed by a doctor
- supervise children in the use of this product
- for athlete's foot: pay special attention to spaces between the toes; wear well-fitting, ventilated shoes, & change shoes & socks at least once daily
- for athlete's foot & ringworm, use daily for 4 weeks; for jock itch, use daily for 2 weeks
- if conditions persist longer, consult a doctor
- this product is not effective on the scalp or nails

Other information

- store between 59º - 86ºF
- lightly shake bottle to loosen settled powder

Inactive ingredients

ZEA MAYS (CORN) STARCH, TRICALICUM PHOSPHATE, MICROCRYSTALLINE CELLULOSE, SODIUM BICARBONATE, ALLANTOIN, CHLOROXYLENOL, FRAGRANCE

Questions?

Call 1-866-964-0939

RECENT MAJOR CHANGES

.

Principal Display Panel

DISCOUNT

drug

mart

FOOD MARKET

Miconazorb AF

Micronazole Nitrate 2% /

Antifungal

ANTIFUNGAL POWDER

- Cures most athlete's

foot, jock itch &

ringworm

- Relieves itching,

burning, scaling, &

chafing

- Comforts & refreshes
- Absorbs moisture
- Talc-free

NET WT. 2.5 OZ. (71g)